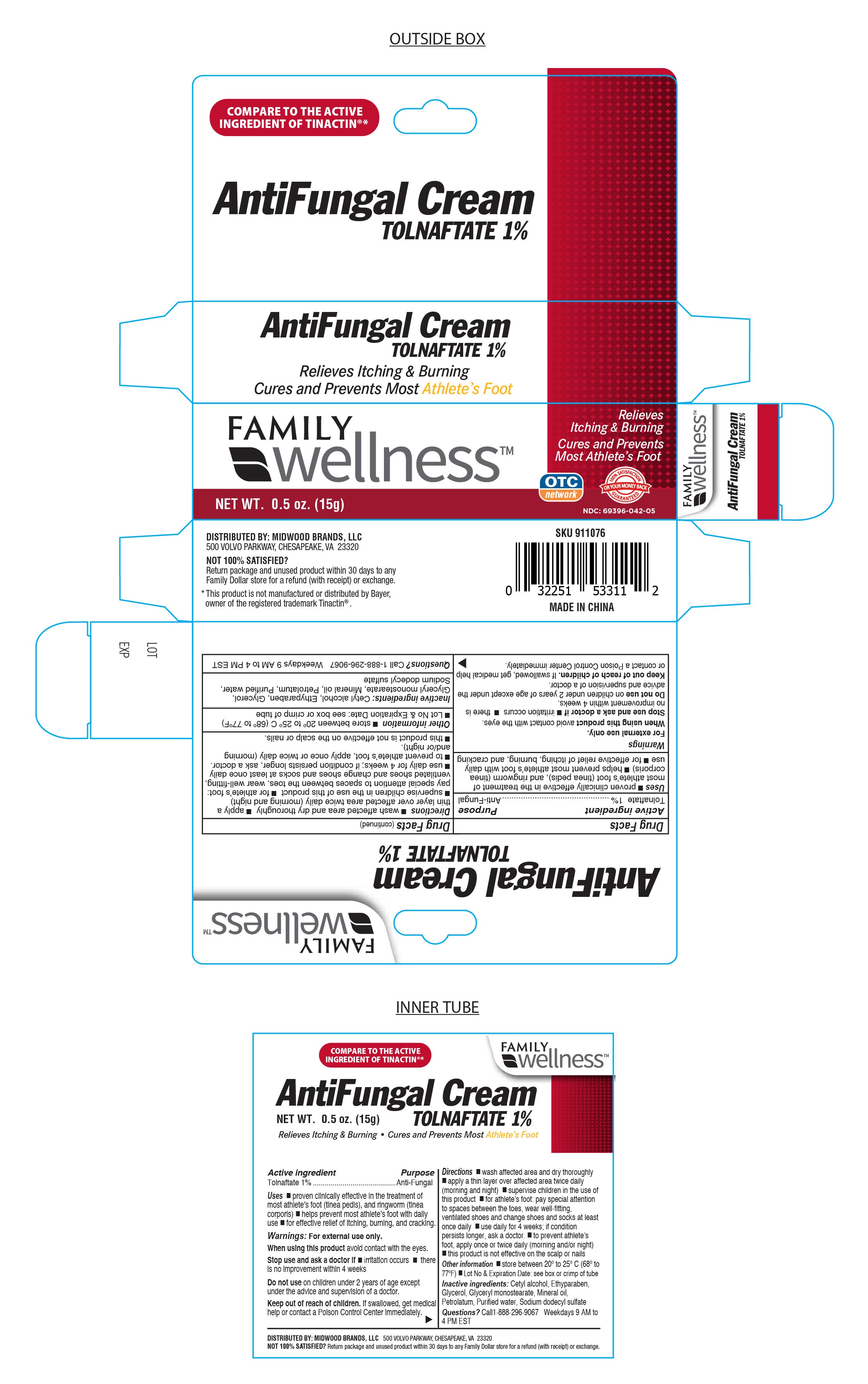 DRUG LABEL: Tolnaftate Cream 1% ANTIFUNGAL
NDC: 69396-042 | Form: CREAM
Manufacturer: Trifecta Pharmaceuticals USA, LLC
Category: otc | Type: HUMAN OTC DRUG LABEL
Date: 20241220

ACTIVE INGREDIENTS: TOLNAFTATE 1 g/100 g
INACTIVE INGREDIENTS: ETHYLPARABEN; GLYCERIN; LIGHT MINERAL OIL; GLYCERYL MONOSTEARATE; PETROLATUM; WATER; SODIUM DODECYLBENZENESULFONATE; CETYL ALCOHOL

ANTIFUNGAL CREAM Tolnaftate 1%

Active ingredient

Tolnaftate 1%

Purpose

Anti-Fungal

Uses

● proven clinically effective in the treatment of most athlete's foot (tinea pedis), and ringworm (tinea corporis) ● helps prevent most athlete's foot with daily use ● for effective relief of itching, burning and cracking.

Warnings

For external use only.

When using this product avoid contact with the eyes.

Stop use and ask a healthcare professional if ● irritation occurs ● there is no improvement within 4 weeks improvement

Do not use on children under 2 years of age except under the advice and supervision of a doctor.

Directions

● wash affected area and dry thoroughly

● apply a thin layer over affected area twice daily (morning and night)

● supervise children in the use of this product

● for athlete’s foot: pay special attention to spaces between the toes, wear well-fitting ventilated shoes and change shoes and socks at least once daily.

● use daily for 4 weeks; if conditions persists longer, ask a doctor.

● to prevent athlete's foot, apply once or twice daily (morning and/or night)

● this product is not effective on the scalp or nails.

Inactive ingredients

Cetyl alcohol, ethylparaben, glycerol, light mineral oil, glycerol monostearate, petrolatum, purified water, sodium dodecyl sulfate

Other information

● store between 20° to 25°C (68° to 77°F) ● Lot No & Expiration Date: See box or crimp of tube.

DISTRIBUTED BY: MIDWOOD BRANDS, LLC.

500 VOLVO PARKWAY, CHESAPEAKE, VA. 23320

NOT SATISFIED?

Return package and unused product within 30 days to any Family Dollar store for a refund (with receipt) or exchange.

This product is not manufactured or distributed by Bayer, owner of the registered trademark Tinactin®